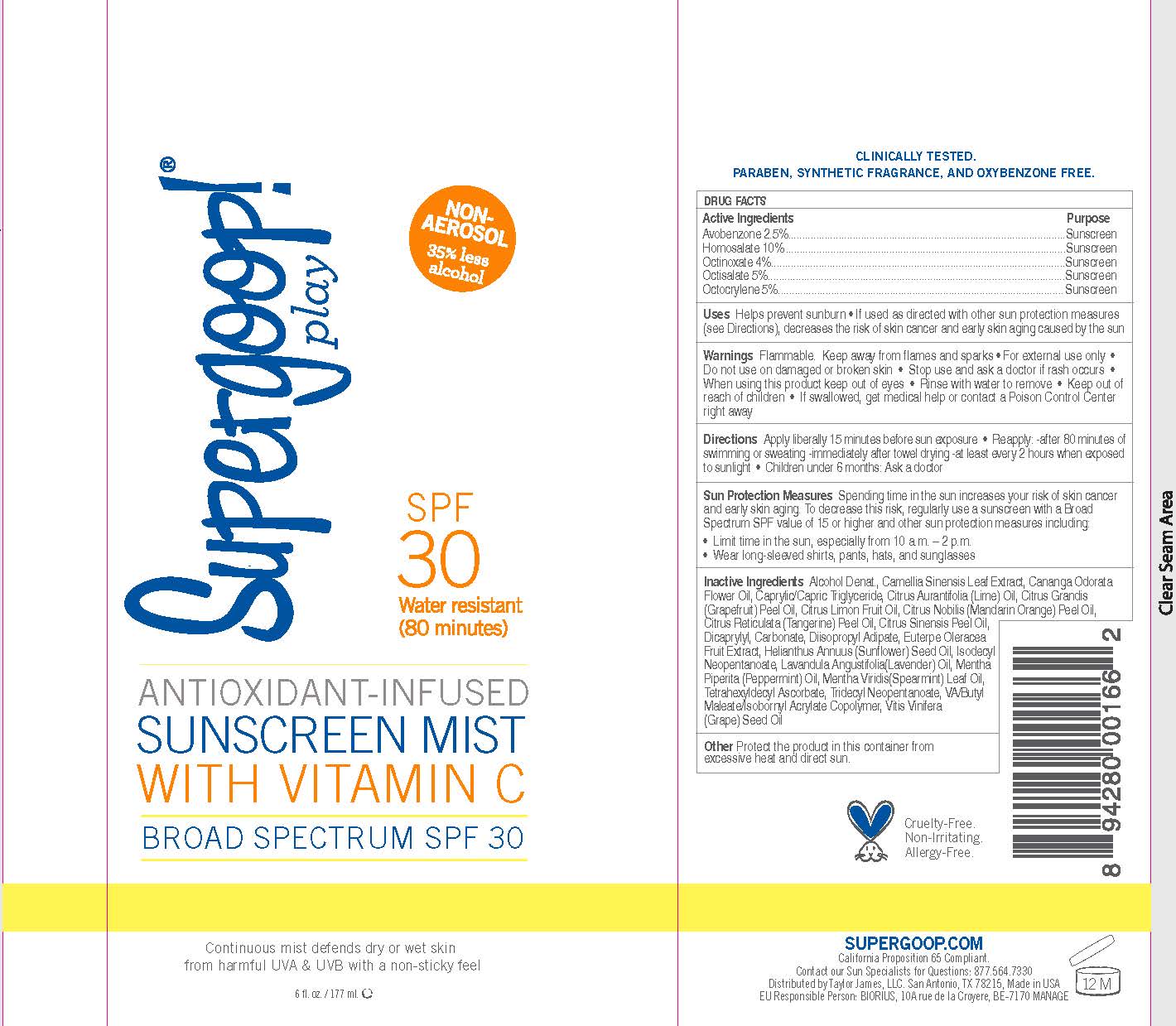 DRUG LABEL: Sunscreen Mist Broad Spectrum SPF 30
NDC: 75936-123 | Form: SPRAY
Manufacturer: TAYLOR JAMES, LTD.
Category: otc | Type: HUMAN OTC DRUG LABEL
Date: 20170120

ACTIVE INGREDIENTS: AVOBENZONE 3 g/100 mL; HOMOSALATE 10 g/100 mL; OCTINOXATE 7.5 g/100 mL; OCTISALATE 5 g/100 mL; OCTOCRYLENE 10 g/100 mL
INACTIVE INGREDIENTS: GREEN TEA LEAF; CANANGA OIL; MEDIUM-CHAIN TRIGLYCERIDES; LIME OIL; CITRUS MAXIMA FRUIT RIND OIL; CITRUS LIMON FRUIT OIL; MANDARIN OIL; ORANGE OIL TERPENELESS; DICAPRYLYL CARBONATE; DIISOPROPYL ADIPATE; ACAI; SUNFLOWER OIL; ISODECYL NEOPENTANOATE; LAVENDER OIL; PEPPERMINT OIL; SPEARMINT OIL; TETRAHEXYLDECYL ASCORBATE; TRIDECYL NEOPENTANOATE; GRAPE SEED OIL

Sunscreen Mist Broad Spectrum SPF 30

Active Ingredients Purpose

Avobenzone 3% Sunscreen

Homosalate 10% Sunscreen

Octinoxate 7.5% Sunscreen

Octisalate 5% Sunscreen

Octocrylene 10% Sunscreen

Uses

Helps Prevent Sunburn

If used as directed with other sun protection measures (see directions), decreases the risk of skin cancer and early skin aging caused by the sun

Keep out of reach of children.

Stop use and ask a doctor if rash occurs

Warnings Flamamble. Keep away from flames and sparks

For external use only

Do not use on damaged or broken skin.

When using this product keep out of eyes. rinse with water to remove

If swallowed, get medical help or contact a Poison Control Center right away.

DOSAGE AND ADMINISTRATION

Directions Apply Liberally 15 minutes before sun exposure

Reapply: after 80 minutes of swimming or sweating

immediately after towel drying

at least every 2 hours when exposed to sunlight

children under 6 months: Ask a doctor

Sun Protection Measures Spending time in the sun increases your risk of skin cancer and early skin aging. To decrease this risk, regularly use a sunscreen with a Broad Spectrum SPF value of 15 or higher and other sun protection measures including:

limit time in the sun, especially from 10 a.m.-2p.m.

wear long-sleved shirts, pants, hats, and sunglasses

INACTIVE INGREDIENT

Inactive Ingredients Alcohol Denat, Camellia Sinensis Leaf Extract, Cananga Odorata Flower Oil, Caprylic/Capric Triglyceride, Citrus Aurantifolia (Lime) Oil, Citrus Grandis (Grapefruit) Peel Oil, Citrus Limon Fruit Oil, Citrus Nobilis (Mandarin Orange) Peel Oil, Citrus Reticulata (Tangerine) Peel Oil, Citrus Sinensis Peel Oil, Dicaprylyl Carbonate, Diisopropyl Adipate, Euterpe Oleracea Fruit Extract, Helianthus Annuus (Sunflower) Seed Oil, Isodecyl Neoppentanoate, Lavandula Angustifolia (lavender) Oil, Mentha Piperita (Peppermint Oil) Mentha Viridis (Spearmint) Leaf Oil, Tetrahexyldecyl Ascorbate (Vitamin C), Tridecyl Neopentanoate, VA/Butyl Maleate/Isobornyl Acrylate Coploymer, Vitis Vinifera (Grape) Seed Oil.

PACKAGE LABEL

Supergoop! Antioxidant-infused

Sunscreen Mist

with Vitamin C

Broad Spectrum SPF 30

Water resistant (80 minutes)

apply to wet or dry skin

Twist-lock cap

6 fl. oz./177 ml